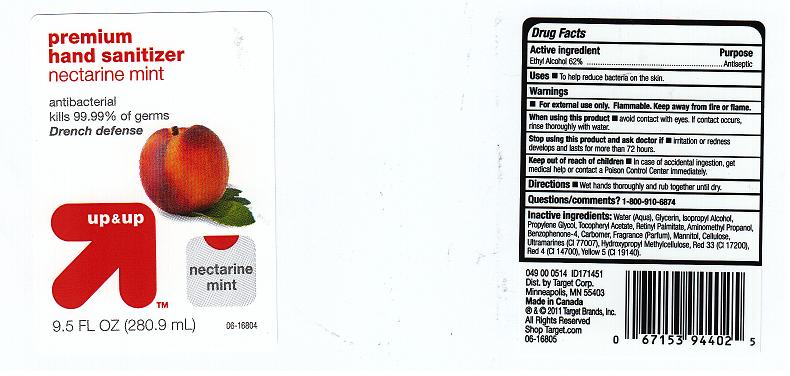 DRUG LABEL: PREMIUM HAND SANITIZER
NDC: 11673-263 | Form: GEL
Manufacturer: TARGET
Category: otc | Type: HUMAN OTC DRUG LABEL
Date: 20110321

ACTIVE INGREDIENTS: ALCOHOL 62 mL/100 mL
INACTIVE INGREDIENTS: WATER; GLYCERIN; ISOPROPYL MYRISTATE; PROPYLENE GLYCOL; .ALPHA.-TOCOPHEROL ACETATE, D-; VITAMIN A PALMITATE; AMINOMETHYLPROPANOL; SULISOBENZONE; CARBOMER 934; MANNITOL; POWDERED CELLULOSE; HYPROMELLOSES; D&C RED NO. 33; FD&C RED NO. 4; FD&C YELLOW NO. 5

DRUG FACTS

ACTIVE INGREDIENT

ETHYL ALCOHOL 62%

PURPOSE

ANTISEPTIC

USES

TO HELP REDUCE BACTERIA ON THE SKIN.

WARNINGS

FOR EXTERNAL USE ONLY. FLAMMABLE. KEEP AWAY FROM FIRE OR FLAME.

WHEN USING THIS PRODUCT

AVOID CONTACT WITH EYES. IF CONTACT OCCURS, RINSE THOROUGHLY WITH WATER.

STOP USING THIS PRODUCT AND ASK DOCTOR IF

IRRITATION OR REDNESS DEVELOPS AND LASTS FOR MORE THAN 72 HOURS.

KEEP OUT OF REACH OF CHILDREN

IN CASE OF ACCIDENTAL INGESTION, GET MEDICAL HELP OR CONTACT A POISON CONTROL CENTER IMMEDIATELY.

DIRECTIONS

WET HANDS THOROUGHLY AND RUB TOGETHER UNTIL DRY.

QUESTIONS OR COMMENTS

1-800-910-6874

INACTIVE INGREDIENTS

WATER, GLYCERIN, ISOPROPYL ALCOHOL, PROPYLENE GLYCOL, TOCOPHERYL ACETATE, RETINYL PALMITATE, AMINOMETHYL PROPANOL, BENZOPHENONE-4, CARBOMER, FRAGRANCE, MANNITOL, CELLULOSE, HYDROXYPROPYL METHYLCELLULOSE, RED 33 (CI 17 200), RED 4 (CI 14700), YELLOW 5 (CI 19140).